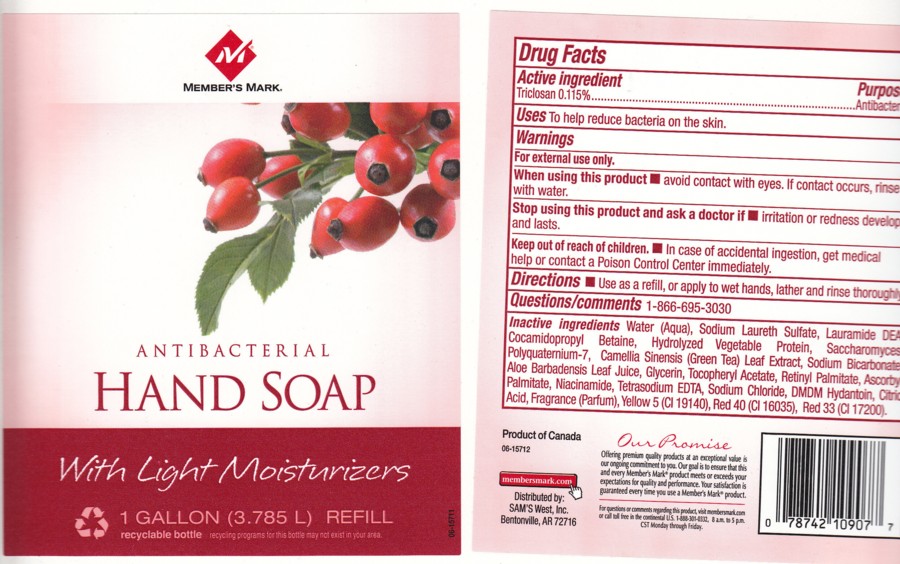 DRUG LABEL: ANTIBACTERIAL HAND SOAP
NDC: 63148-140 | Form: LOTION
Manufacturer: APOLLO HEALTH AND BEAUTY CARE
Category: otc | Type: HUMAN OTC DRUG LABEL
Date: 20100224

ACTIVE INGREDIENTS: TRICLOSAN 0.1150 mL/100 mL

ANTIBACTERIAL HAND SOAP

ACTIVE INGREDIENT

TRICLOSAN 0.115% (ANTIBACTERIAL)

USES

TO HELP REDUCE BACTERIA ON SKIN

WARNINGS

FOR EXTERNAL USE ONLY.

WHEN USING THIS PRODUCT

- AVOID CONTACT WITH EYES.IF CONTACT OCCURS, RINSE WITH WATER.

STOP USING THIS PRODUCT AND ASK A DOCTOR IF

- IRRITATION OR REDNESS DEVELOPS AND LASTS.

KEEP OUT OF REACH OF CHILDREN

- IN CASE OF ACCIDENTAL INGESTION, GET MEDICAL HELP OR CONTACT A POISON CONTROL CENTER IMMEDIATELY.

QUESTIONS/COMMENTS

1-866-695-3030

PACKAGE FRONT AND BACK LABELS

- 140.jpg